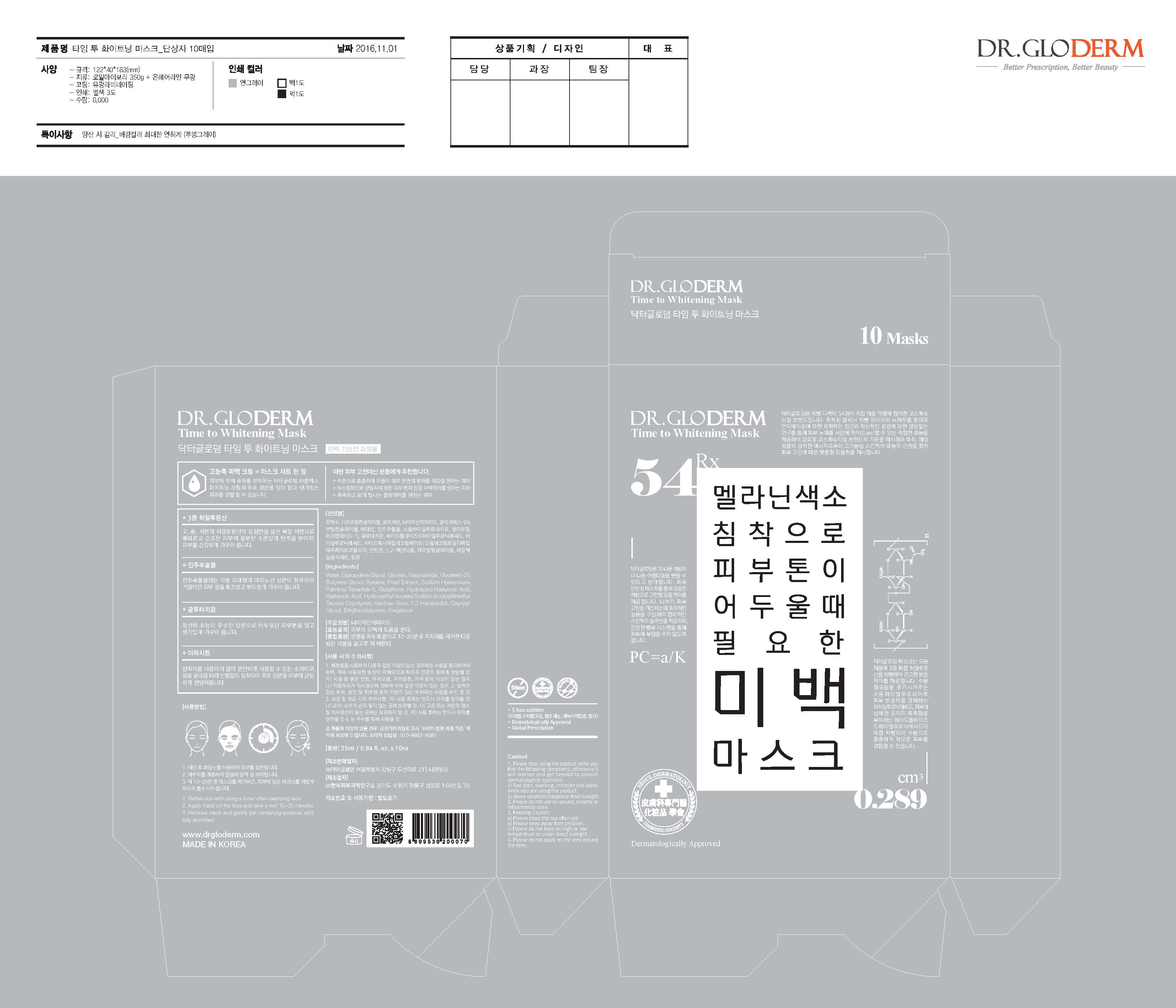 DRUG LABEL: DR. GLODERM TIME TO WHITENING MASK
NDC: 71342-0003 | Form: LIQUID
Manufacturer: DR.GLODERM
Category: otc | Type: HUMAN OTC DRUG LABEL
Date: 20170323

ACTIVE INGREDIENTS: NIACINAMIDE 2 g/100 mL
INACTIVE INGREDIENTS: WATER; BUTYLENE GLYCOL

Drug Facts

ACTIVE INGREDIENT

Niacinamide

INACTIVE INGREDIENT

Water, Glycerin, Sodium Hyaluronate, Butylene Glycol, Pearl Extract, Hydrolyzed Hyaluronic Acid, Hyaluronic Acid, Glutathione, etc.

PURPOSE

Skin Protectant - Whitening

keep out of reach of the children

INDICATIONS AND USAGE

1. Refine skin with using a toner after cleansing face.
2. Apply mask on the face and take a rest 10-20 minutes.
3. Remove mask and gently pat remaining essence until fully absorbed.

WARNINGS

1. If the following symptoms occur after product use, stop using the product immediately and consult a dermatologist (continuous use can exacerbate the symptoms).
1) Occurrence of red spots, swelling, itchiness, and other skin irritation
2) If the symptoms above occur after the application area is exposed to direct sunlight
2. Do not use on open wounds, eczema, and other skin irritations
3. Precaution for Storage and Handling
1) Close the lid after use
2) Keep out of reach of infants and children
3) Do not to store in a place with high/low temperature and exposed to direct sunlight

4. Use as avoiding eye areas.

DOSAGE AND ADMINISTRATION

for external use only